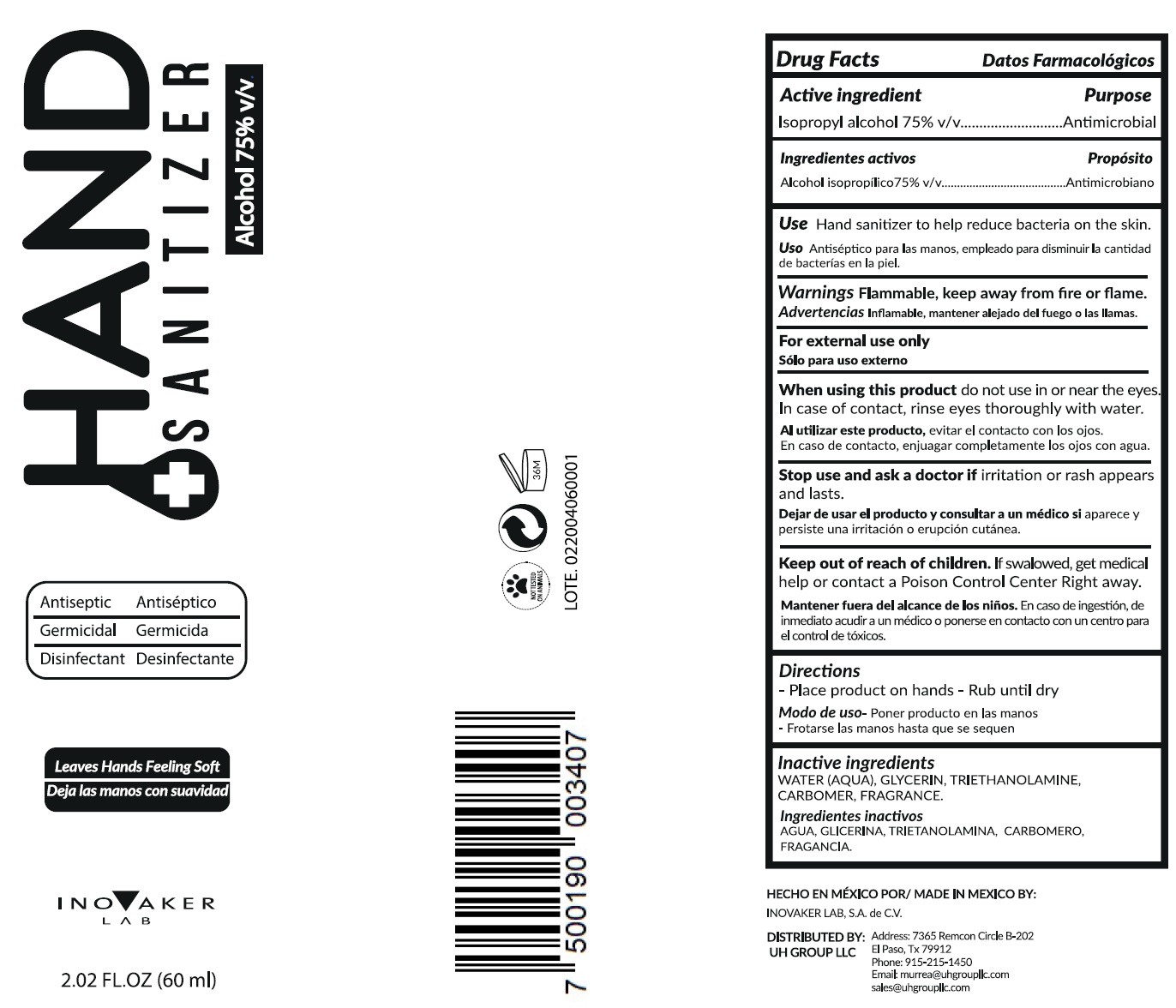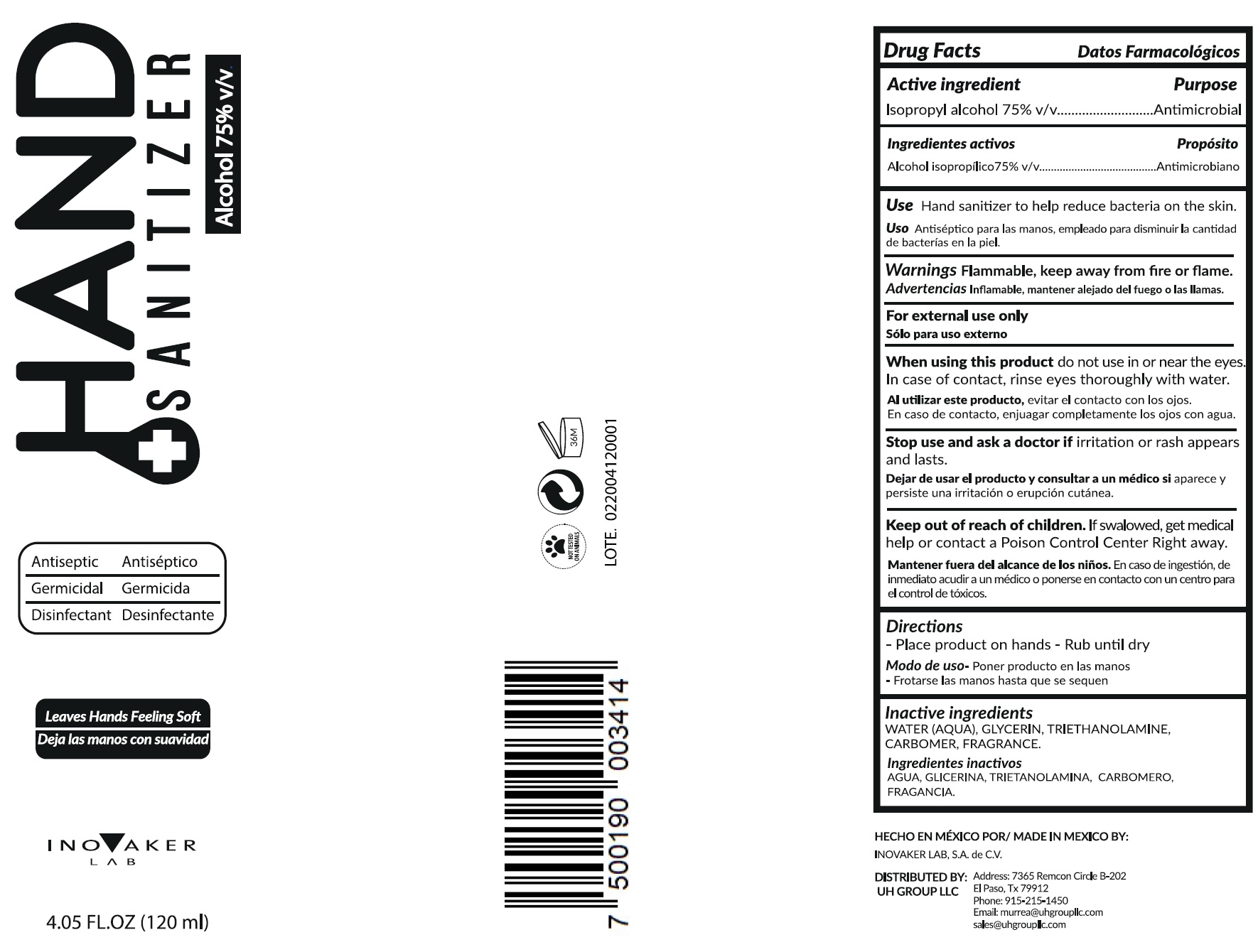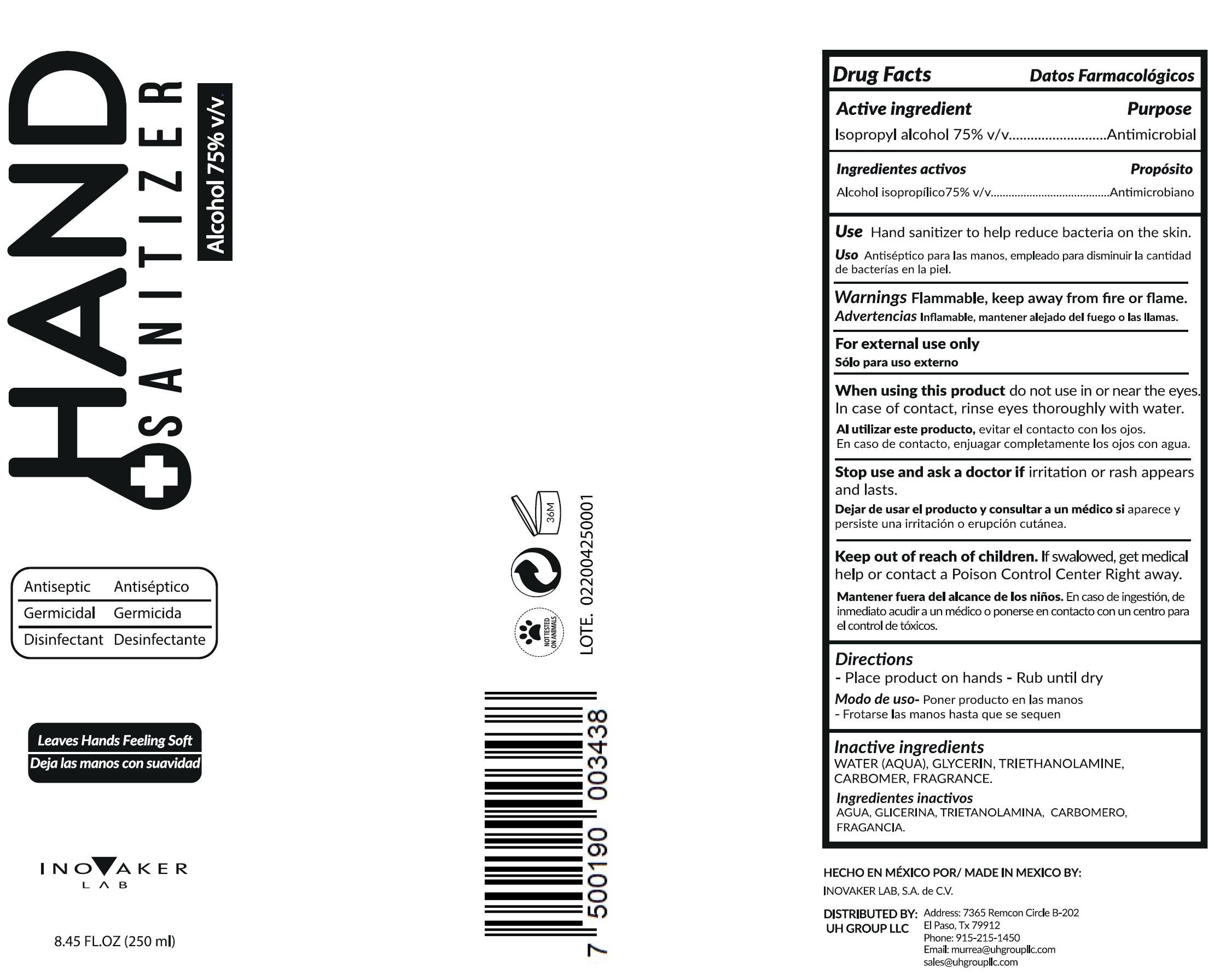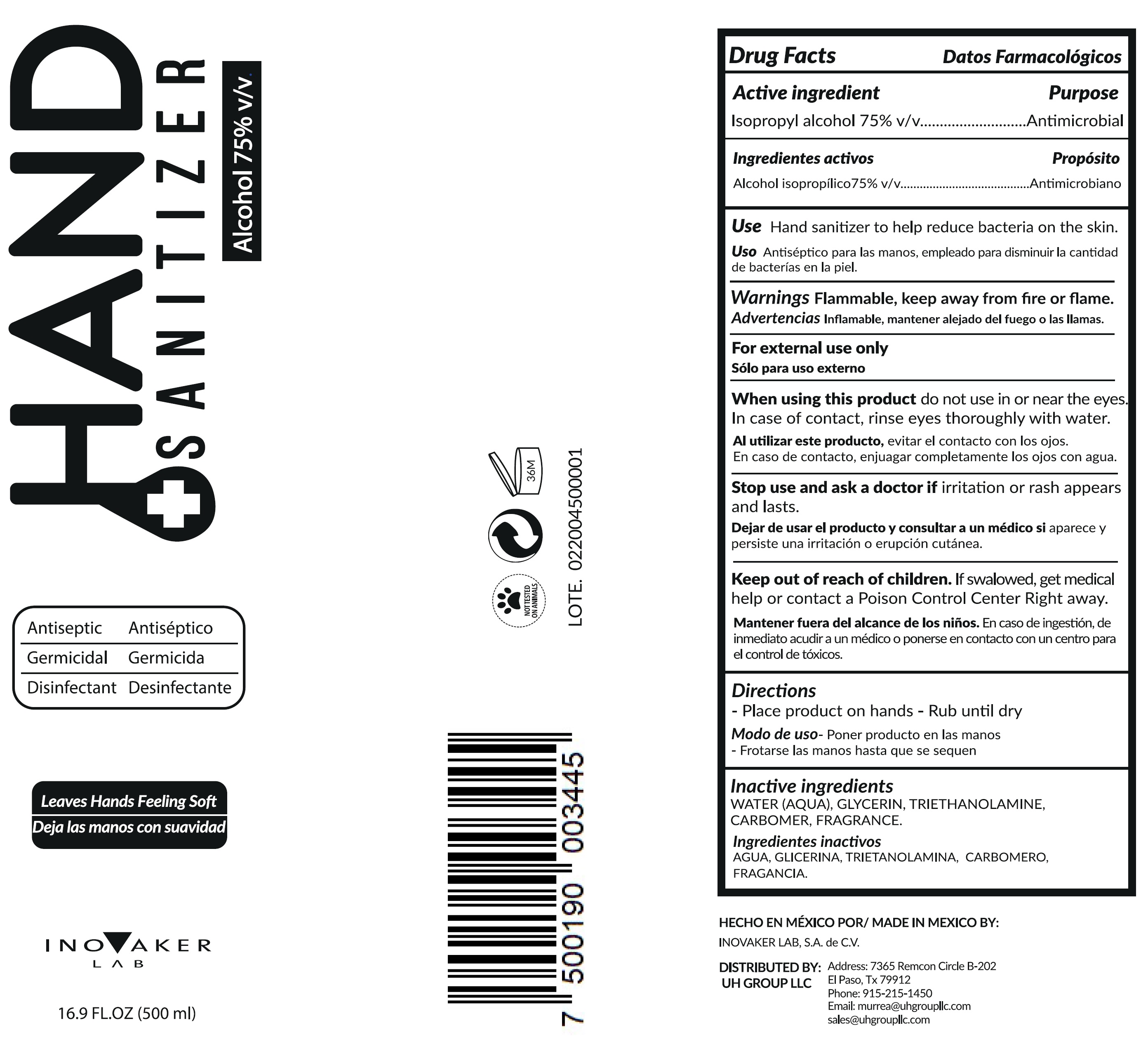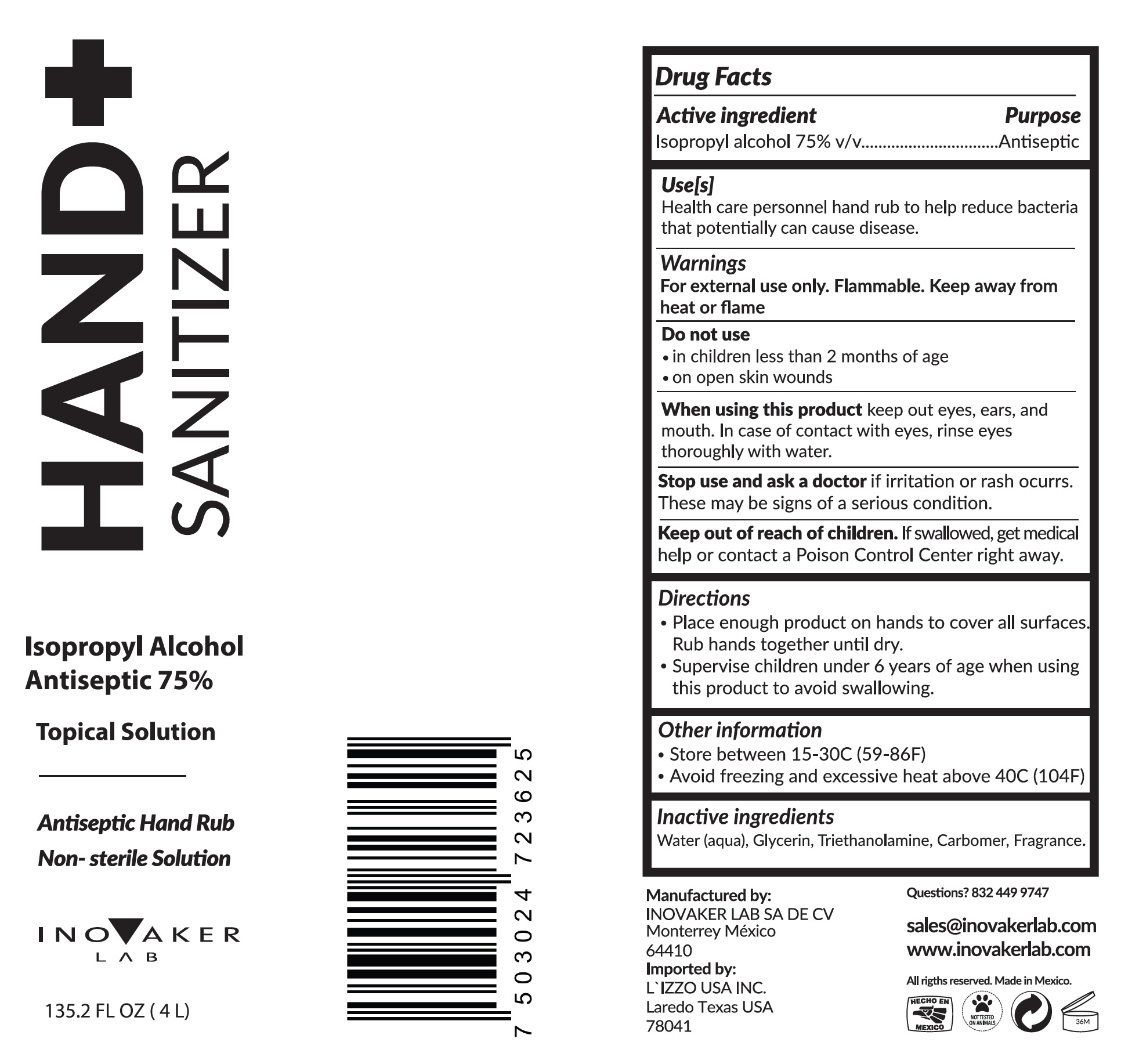 DRUG LABEL: Inovaker Lab Hand Sanitizer
NDC: 78106-002 | Form: GEL
Manufacturer: UH Group LLC
Category: otc | Type: HUMAN OTC DRUG LABEL
Date: 20200727

ACTIVE INGREDIENTS: ISOPROPYL ALCOHOL 0.75 mL/1 mL
INACTIVE INGREDIENTS: WATER; GLYCERIN; TROLAMINE; CARBOMER HOMOPOLYMER, UNSPECIFIED TYPE; FRAGRANCE LAVENDER & CHIA F-153480

Inovaker Lab Hand Sanitizer

Active ingredient

Isopropyl alcohol 75% v/v

Purpose

Antimicrobial

Use

Hand sanitizer to help reduce bacteria on the skin.

Warnings

Flammable, keep away from fire or flame

For external use only

When using this product

do not use in or near the eyes. In case of contact, rinse eyes thoroughly with water.

Stop use and ask a doctor if

irritation or rash appears and lasts.

Keep out of reach of children.

If swalowed, get medical help or contact a Poison Control Center Right away.

Directions

-Place product on hands - Rub until dry

Inactive ingredients

WATER (AQUA), GLYCERIN, TRIETHANOLAMINE, CARBOMER, FRAGRANCE.